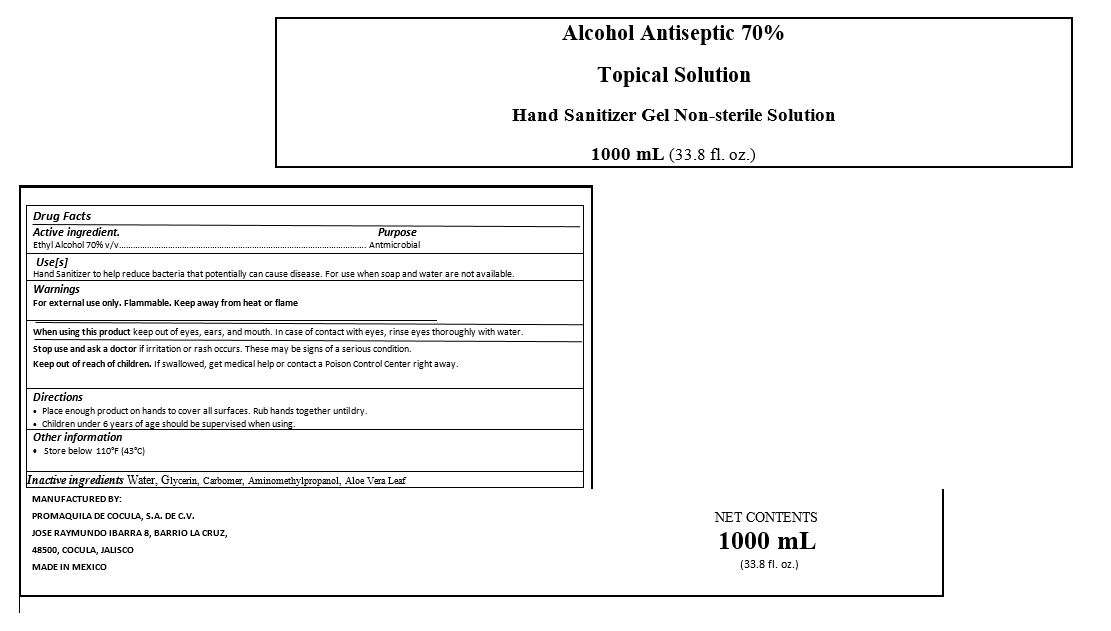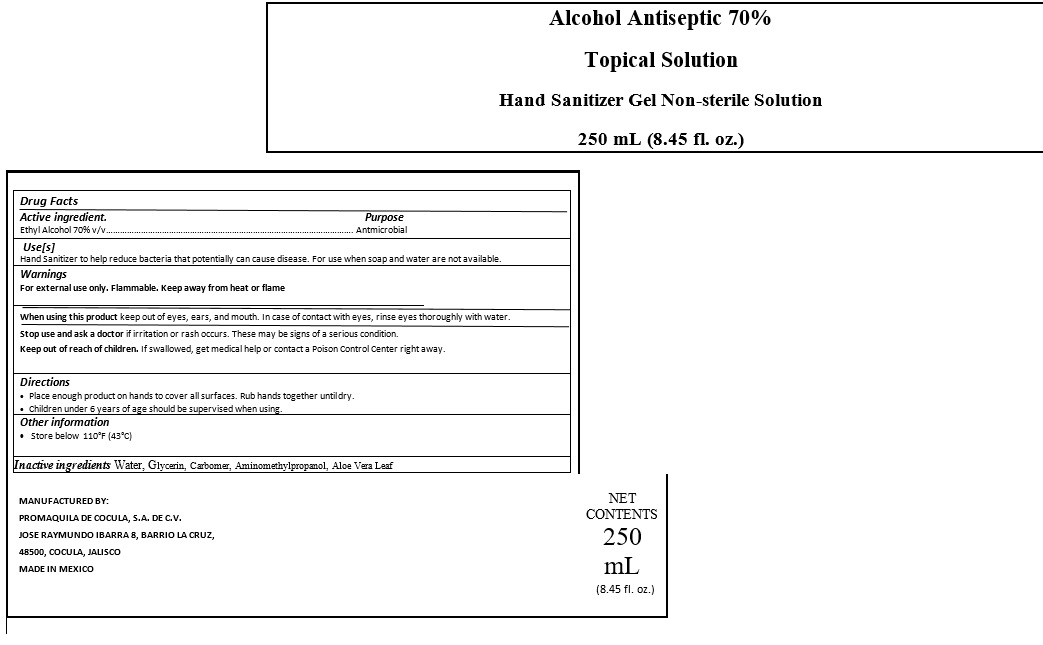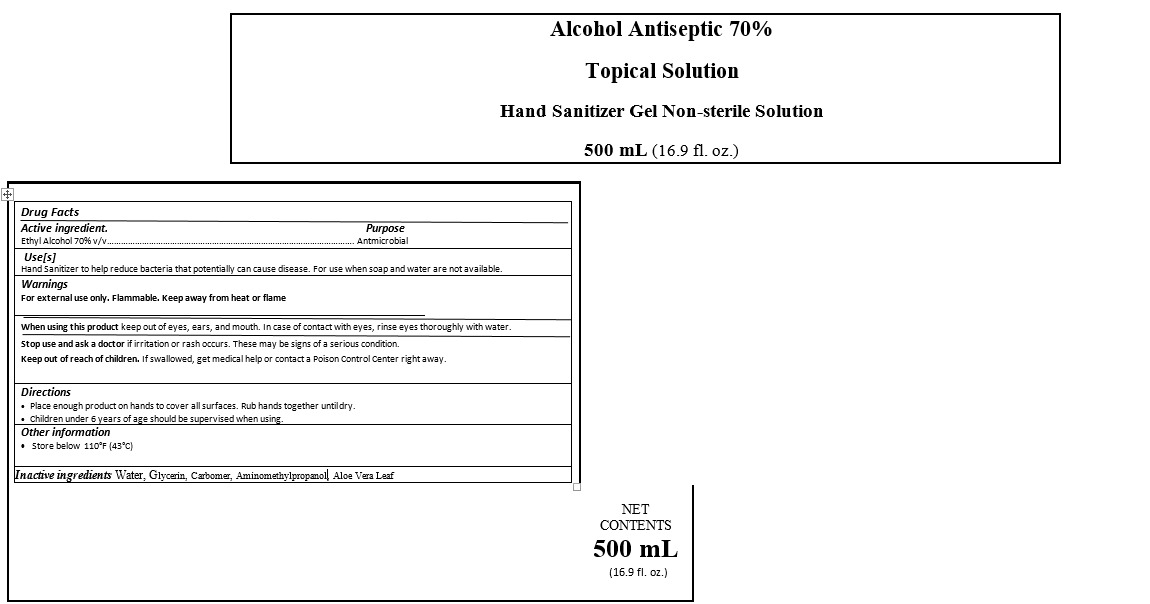 DRUG LABEL: IBARRA
NDC: 79577-0004 | Form: GEL
Manufacturer: PROMAQUILA DE COCULA, S.A. DE C.V.
Category: otc | Type: HUMAN OTC DRUG LABEL
Date: 20200804

ACTIVE INGREDIENTS: ALCOHOL 0.7 mL/1 mL
INACTIVE INGREDIENTS: CARBOMER 940 0.0043 mL/1 mL; WATER 0.28711 mL/1 mL; GLYCERIN 0.00302 mL/1 mL; ALOE VERA LEAF 0.00278 mL/1 mL; AMINOMETHYLPROPANOL 0.00279 mL/1 mL

LAVENDER SCENTED HAND SANITIZER

ACTIVE INGREDIENTS

Active ingredient. Ethyl Alcohol 70%

PURPOSE

Purpose Antmicrobial

INDICATIONS AND USAGE

Use[s]

Hand Sanitizer to help reduce bacteria that potentially can cause disease. For use when soap and water are not available.

Directions

Place enough product on hands to cover all surfaces. Rub hands together until dry.

DOSAGE AND ADMINISTRATION

Place enough product on hands to cover all surfaces. Rub hands together until dry.

WARNINGS AND PRECAUTIONS

When using this product keep out of eyes, ears, and mouth. In case of contact with eyes, rinse eyes thoroughly with water.

Children under 6 years of age should be supervised when using.

STOP USE

Stop use and ask a doctor if irritation or rash occurs. These may be signs of a serious condition.

Keep out of reach of children. If swallowed, get medical help or contact a Poison Control Center right away.

INACTIVE INGREDIENTS

Inactive ingredients Water, Glycerin, Carbomer, Triethanolamine, Aloe Vera Leaf,